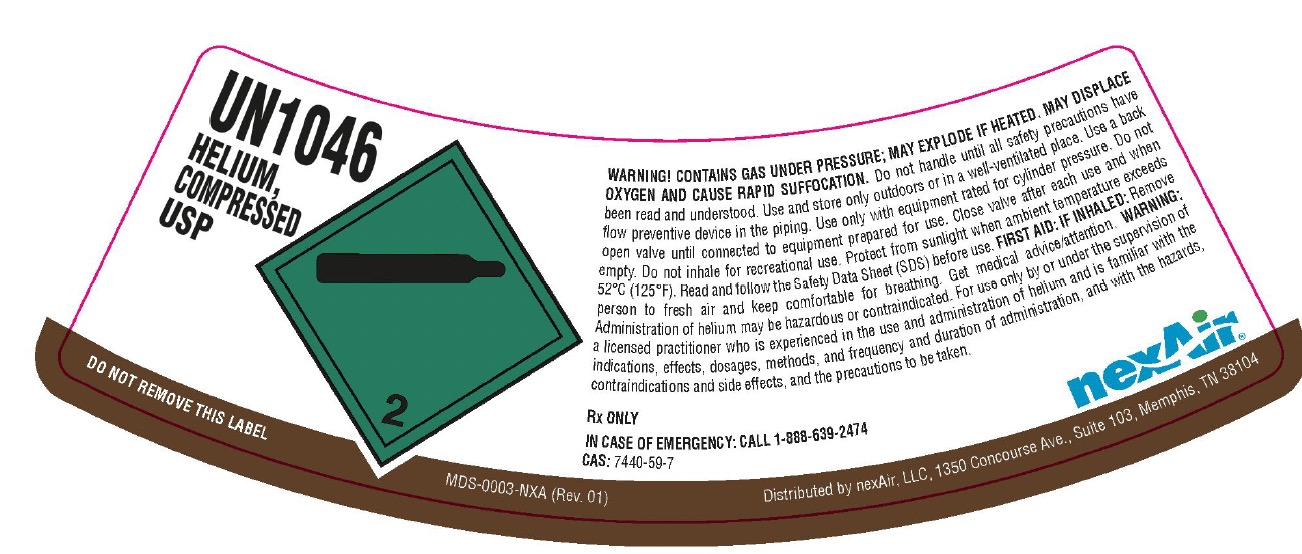 DRUG LABEL: Helium
NDC: 12213-712 | Form: GAS
Manufacturer: NexAir, LLC
Category: animal | Type: PRESCRIPTION ANIMAL DRUG LABEL
Date: 20251111

ACTIVE INGREDIENTS: Helium 999 mL/1 L

Helium Label

PACKAGE LABEL

UN1046
HELIUM, COMPRESSED USP
DO NOT REMOVE THIS LABEL
WARNING! CONTAINS GAS UNDER PRESSURE; MAY EXPLODE IF HEATED. MAY DISPLACE OXYGEN AND CAUSE RAPID SUFFOCATION. Do not handle until all safety precautions have been read and understood. Use and store only outdoors or in a well-ventilated place. Use a back flow preventive device in the piping. Use only with equipment rated for cylinder pressure. Do not open valve until connected to equipment prepared for use. Close valve after each use and when empty. Do not inhale for recreational use. Protect form sunlight when ambient temperature exceeds 52 C (125 F). Read and follow the Safety Data Sheet (SDS) before use. FIRST AIR: IF INHALED: Remove person to fresh air and keep comfortable for breathing. Get medical advice/attention. WARNING: Administration of helium may be hazardous or contraindicated. For use only by or under the supervision of a licensed practitioner who is experienced in the use and administration of helium and is familiar with the indications, effects, dosages, methods, and frequency and duration of administration, and with the hazards, contraindications and side effects, and the precautions to be taken.
Rx ONLY
IN CASE OF EMERGENCY: CALL 1-888-639-2474
CAS: 7440-59-7
nexAir
Distributed by nexAir, LLC, 1350 Concourse Ave., Suite 103, Memphis, TN 38104